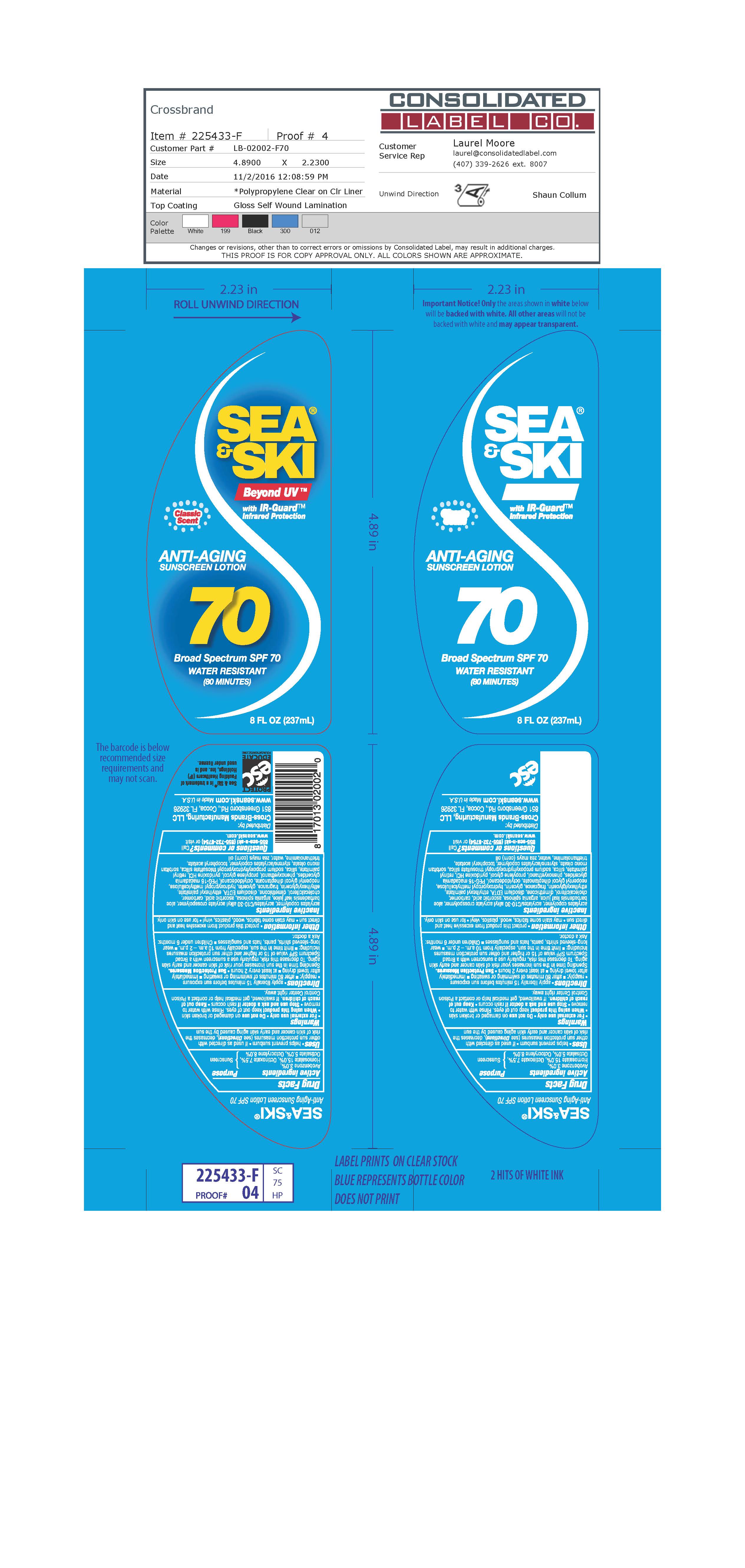 DRUG LABEL: General Protection
NDC: 71153-2002 | Form: LOTION
Manufacturer: Cross-Brand Manufacturing, LLC
Category: otc | Type: HUMAN OTC DRUG LABEL
Date: 20161222

ACTIVE INGREDIENTS: OCTINOXATE 7.5 g/1 mL; OCTISALATE 5 g/1 mL; OCTOCRYLENE 8 g/1 mL; HOMOSALATE 15 g/1 mL; AVOBENZONE 3 g/1 mL
INACTIVE INGREDIENTS: ALOE VERA LEAF

Sea & Ski Sunscreen Lotion SPF 70